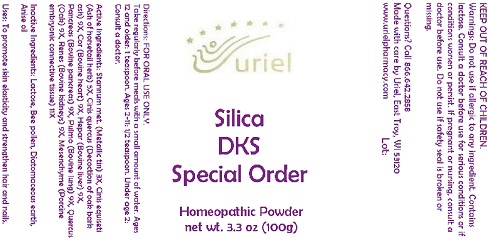 DRUG LABEL: Silica
NDC: 48951-8317 | Form: POWDER
Manufacturer: Uriel Pharmacy Inc
Category: homeopathic | Type: HUMAN OTC DRUG LABEL
Date: 20170724

ACTIVE INGREDIENTS: EQUISETUM ARVENSE TOP 5 [hp_X]/1 1; WHITE OAK BARK 9 [hp_X]/1 1; MAMMAL LIVER 9 [hp_X]/1 1
INACTIVE INGREDIENTS: LACTOSE; POLLEN; ANISE OIL

Silica Powder - 120 ml

Purpose

Uses: To promote skin elasticity and strengthen hair and nails.

Dosage & Administration

Directions: Take regularly before meals with a small amount of water. Ages 12 and older: 1 tsp. Ages 2-11: 1/2 tsp. Under age 2: Ask a doctor.

OTC-Active Ingredient

Active Ingredients: Stannum met. (Metallic tin) 3X, Cinis equiseti (Ash of horsetail herb) 5X, Cinis quercus (Decoction of oak bark ash) 9X, Cor (Bovine heart) 9X, Hepar (Bovine liver) 9X, Pancreas (Bovine pancreas) 9X, Pulmo (Bovine lung) 9X, Quercus (Oak) 9X, Renes (Bovine kidneys) 9X, Mesenchyme (Porcine embryonic connective tissue) 11X

Inactive Ingredient

Inactive Ingredients: Lactose, Bee pollen, Diatomaceous earth, Anise oil, Mesenchyme, Pancreas, Pulmo, Cor, Renes.

Keep out of reach of children

Do not use if allergic to any ingredient. Do not use if safety seal is broken or missing.

Warnings: Do not use if allergic to any ingredient. Do not use if safety seal is broken or missing.

Ask doctor section

Consult your doctor if you are lactose intolerant.

Pregnancy or breast feeding section

If you are pregnant or nursing, consult a doctor before use.

Questions section

Made with care by
Uriel Pharmacy
East Troy, WI 53120
Questions or comments?
Please call 1.866.642.2858
www.urielpharmacy.com